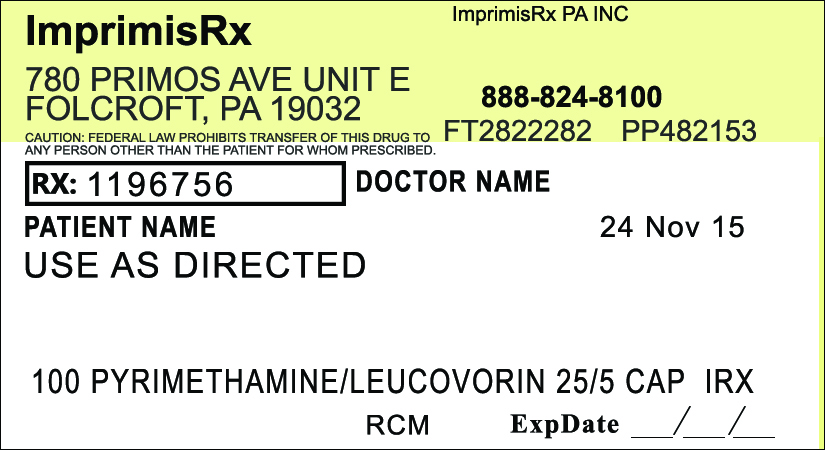 DRUG LABEL: Pyrimethamine Leucovorin
NDC: 70271-426 | Form: CAPSULE
Manufacturer: ImprimisRx PA, Inc. d/b/a ImprimisRx
Category: prescription | Type: HUMAN PRESCRIPTION DRUG LABEL
Date: 20151127

ACTIVE INGREDIENTS: PYRIMETHAMINE 25 mg/1 1; LEUCOVORIN CALCIUM 5 mg/1 1
INACTIVE INGREDIENTS: CELLULOSE, MICROCRYSTALLINE 90 mg/1 1

Pyrimethamine Leucovorin (25mg-5mg)